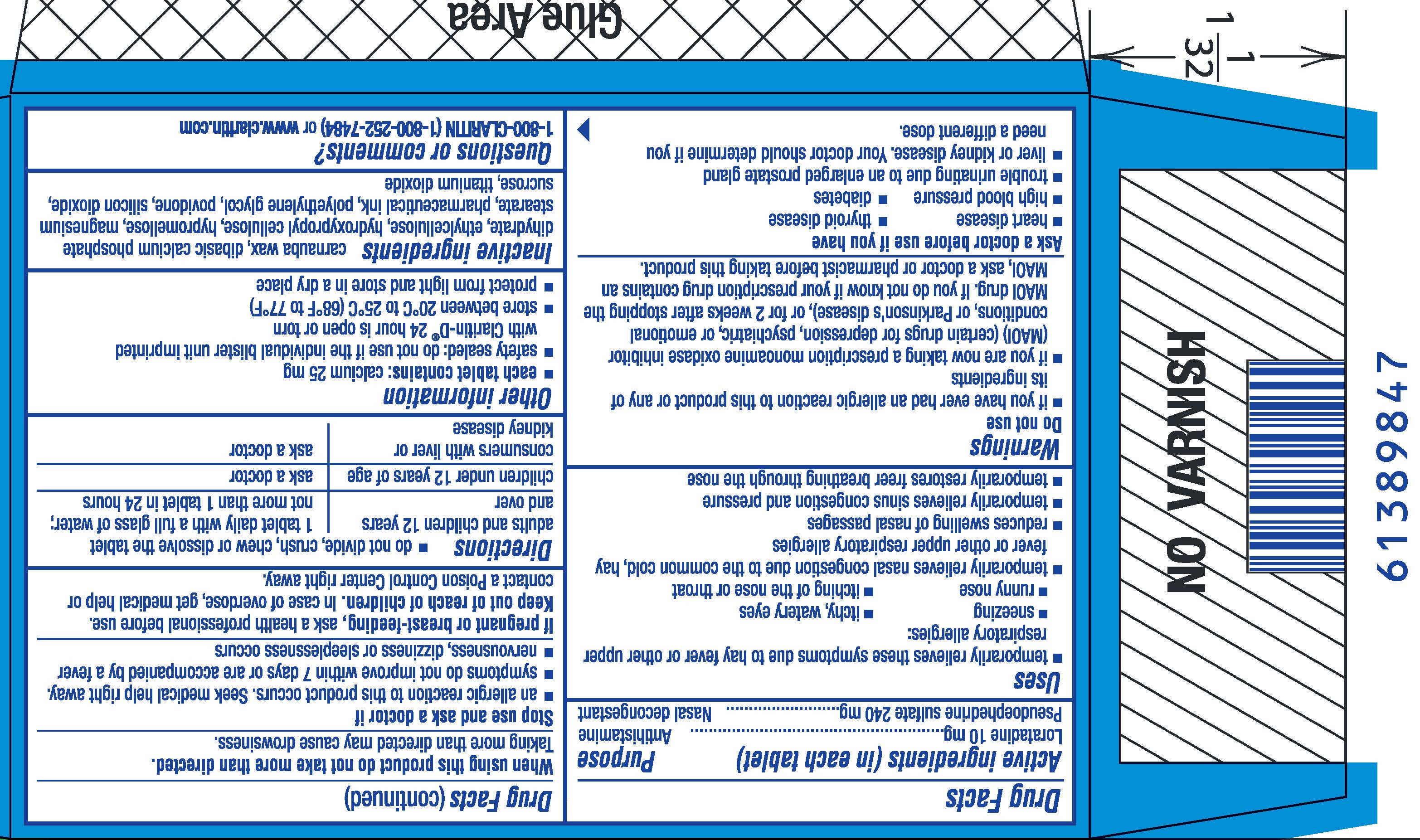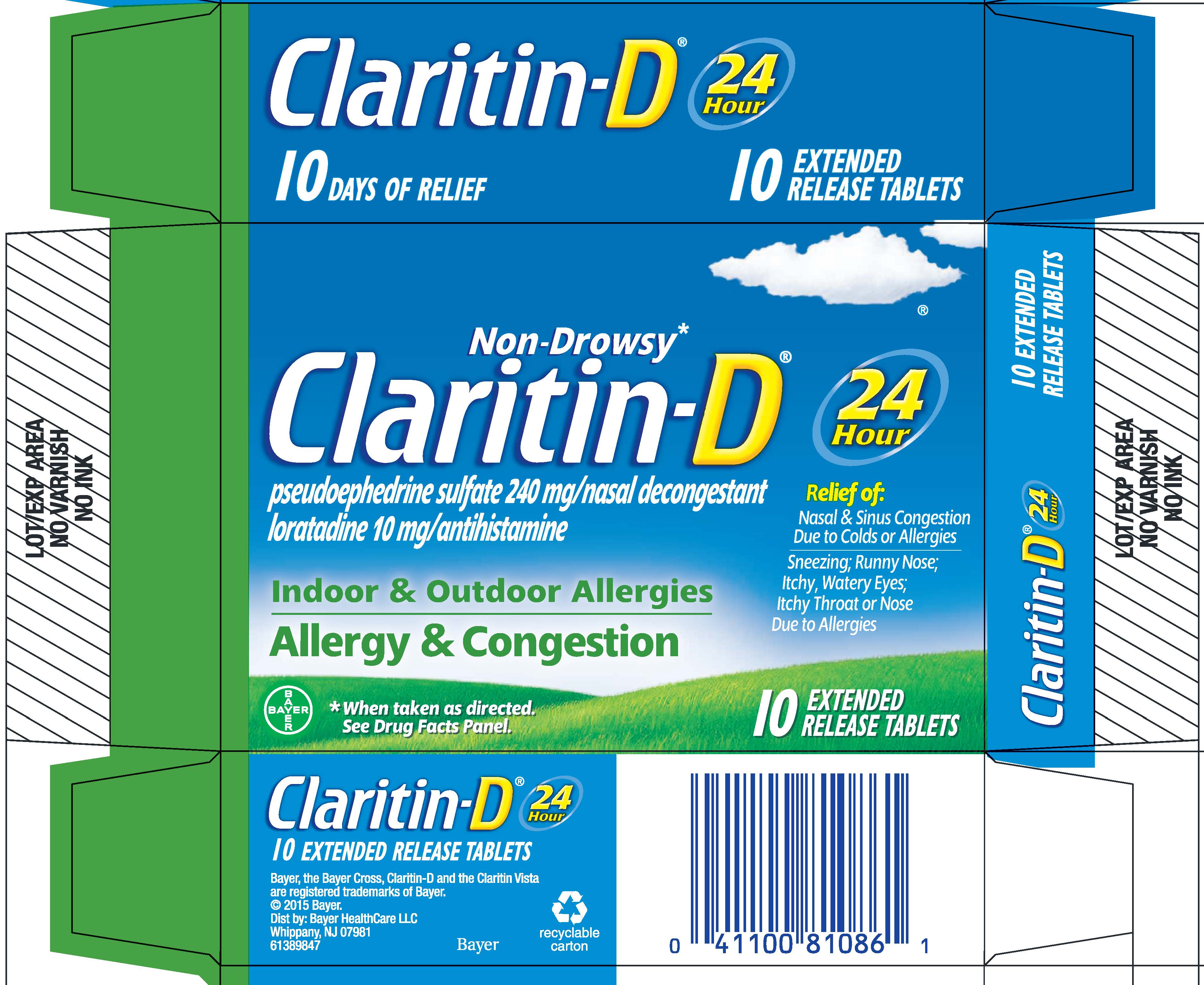 DRUG LABEL: Claritin-D
NDC: 11523-4332 | Form: TABLET, EXTENDED RELEASE
Manufacturer: Bayer HealthCare LLC.
Category: otc | Type: HUMAN OTC DRUG LABEL
Date: 20251205

ACTIVE INGREDIENTS: LORATADINE 10 mg/1 1; PSEUDOEPHEDRINE SULFATE 240 mg/1 1
INACTIVE INGREDIENTS: CARNAUBA WAX; CALCIUM PHOSPHATE, DIBASIC, DIHYDRATE; HYPROMELLOSES; ETHYLCELLULOSES; HYDROXYPROPYL CELLULOSE (1600000 WAMW); MAGNESIUM STEARATE; POLYETHYLENE GLYCOL, UNSPECIFIED; POVIDONE; SILICON DIOXIDE; SUCROSE; TITANIUM DIOXIDE

Claritin-D®
24 Hour

Drug Facts

ACTIVE INGREDIENT

Active ingredient (in each tablet) | Purpose
Loratadine 10 mg | Antihistamine
Pseudoephedrine sulfate 240 mg | Nasal decongestant

Uses

- temporarily relieves these symptoms due to hay fever or other upper respiratory allergies:
- sneezing
- itchy, watery eyes
- runny nose
- itching of the nose or throat
- temporarily relieves nasal congestion due to the common cold, hay fever or other upper respiratory allergies
- reduces swelling of nasal passages
- temporarily relieves sinus congestion and pressure
- temporarily restores freer breathing through the nose

Warnings

Do not use

- if you have ever had an allergic reaction to this product or any of its ingredients
- if you are now taking a prescription monoamine oxidase inhibitor (MAOI) (certain drugs for depression, psychiatric, or emotional conditions, or Parkinson's disease), or for 2 weeks after stopping the MAOI drug. If you do not know if your prescription drug contains an MAOI, ask a doctor or pharmacist before taking this product.

Ask a doctor before use if you have

- heart disease
- thyroid disease
- high blood pressure
- diabetes
- trouble urinating due to an enlarged prostate gland
- liver or kidney disease. Your doctor should determine if you need a different dose.

When using this product do not take more than directed. Taking more than directed may cause drowsiness.

Stop use and ask a doctor if

- an allergic reaction to this product occurs. Seek medical help right away.
- symptoms do not improve within 7 days or are accompanied by a fever
- nervousness, dizziness or sleeplessness occurs

PREGNANCY OR BREAST FEEDING

If pregnant or breast-feeding, ask a health professional before use.

Keep out of reach of children. In case of overdose, get medical help or contact a Poison Control Center right away.

Directions

- do not divide, crush, chew or dissolve the tablet

adults and children 12 years and over | 1 tablet daily with a full glass of water; not more than 1 tablet in 24 hours
children under 12 years of age | ask a doctor
consumers with liver or kidney disease | ask a doctor

Other information

- each tablet contains: calcium 25 mg
- safety sealed: do not use if the individual blister unit imprinted with Claritin-D® 24 hour is open or torn
- store between 20° to 25°C (68° to 77°F)
- protect from light and store in a dry place

Inactive ingredients

carnauba wax, dibasic calcium phosphate dihydrate, ethylcellulose, hydroxypropyl cellulose, hypromellose, magnesium stearate, pharmaceutical ink, polyethylene glycol, povidone, silicon dioxide, sucrose, titanium dioxide

Questions or comments?

1-800-CLARITIN (1-800-252-7484) or www.claritin.com

PRINCIPAL DISPLAY PANEL - 10 Tablet Blister Pack Carton

NDC 11523-4332-1

Non-Drowsy*
Claritin-D ®
pseudoephedrine sulfate 240 mg/nasal decongestant
loratadine 10 mg/antihistamine

Indoor & Outdoor Allergies
Allergy & Congestion

24
Hour

Relief of:
Nasal & Sinus Congestion
Due to Colds or Allergies
Sneezing; Runny Nose;
Itchy, Watery Eyes;
Itchy Throat or Nose
Due to Allergies

* When taken as directed. See Drug Facts Panel.

5
EXTENDED
RELEASE TABLETS